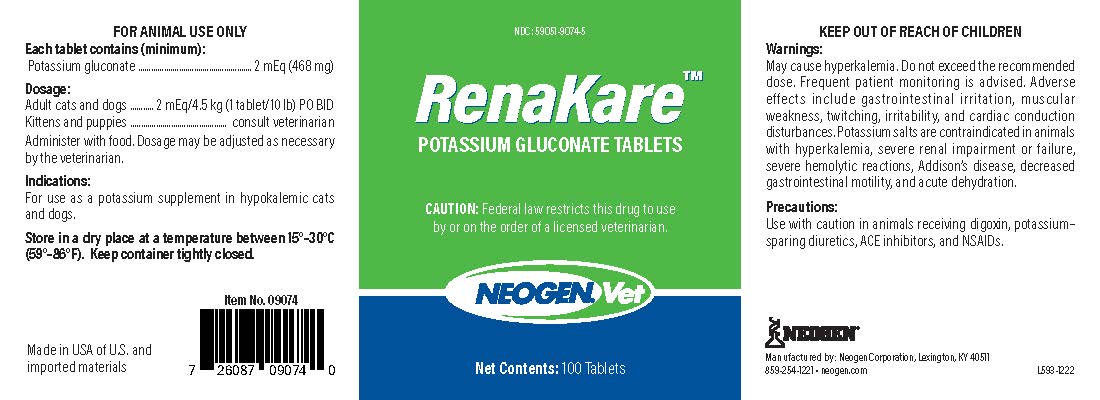 DRUG LABEL: RenaKare
NDC: 59051-9074 | Form: TABLET
Manufacturer: Neogen Corporation-Mercer
Category: animal | Type: PRESCRIPTION ANIMAL DRUG LABEL
Date: 20230221

ACTIVE INGREDIENTS: POTASSIUM GLUCONATE 468 mg/1 1

DESCRIPTION

RenaKare™

Potassium Gluconate Tablets

CAUTION: Federal law restricts this drug to use by or on the order of a licensed veterinarian.

FOR ANIMAL USE ONLY

KEEP OUT OF REACH OF CHILDREN

Each tablet contains (minimum):

Potassium gluconate.........2 mEq (468 mg)

Dosage:

Adult cats and dogs...2 mEq/4.5 kg (1 tablet/10 lb) PO BID

Kittens and puppies.............................consult veterinarian

Administer with food. Dosage may be adjusted as necessary by the veterinarian.

STORAGE AND HANDLING

Store in a dry place at a temperature between 15°-30°C (59°-86°F). Keep container tightly closed.

Warnings:

May cause hyperkalemia. Do not exceed the recommended dose. Frequent patient monitoring is advised. Adverse effects include gastrointestinal irritation, muscular weakness, twitching, irritability, and cardiac conduction disturbances. Postassium salts are contraindicated in animals with hyperkalemia, severe renal impairment or failure, severe hemolytic reactions, Addison's disease, decreased gastrointestinal motility, and acute dehydration.

Precautions:

Use with caution in animals receiving digoxin, potassium-sparing diuretics, ACE inhibitors, and NSAIDs.

Indications:

For use as a potassium supplement in hypokalemic cats and dogs.

Manufactured by: Neogen Corporation, Lexington, KY 40511

859-254-1221 • neogen.com L593-1222

Made in the USA of U.S. and imported materials

Item No. 09074

PRINCIPAL DISPLAY PANEL - 100 Tablet Bottle

NDC: 59051-9074-5

RenaKare

Potassium gluconate tablets

CAUTION: Federal law restricts this drug to use by or on the order of a licensed veterinarian.

Net Contents: 100 Tablets